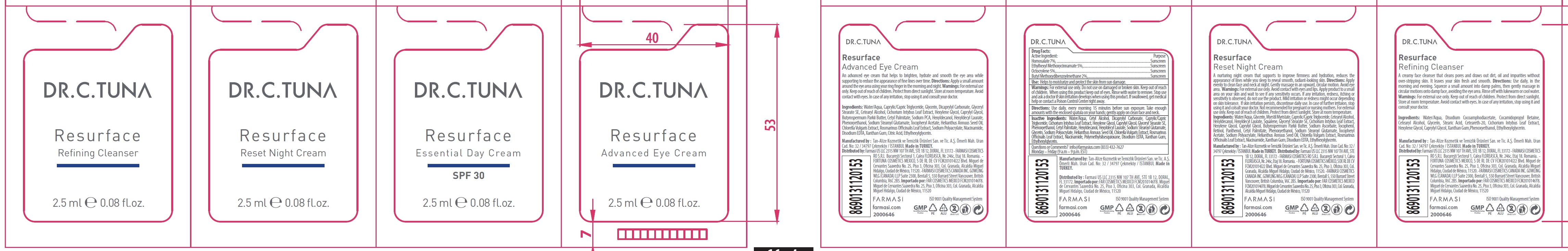 DRUG LABEL: Dr. C. Tuna Resurface Essential Day Cream SPF 30
NDC: 74690-025 | Form: KIT | Route: TOPICAL
Manufacturer: Farmasi US LLC
Category: otc | Type: HUMAN OTC DRUG LABEL
Date: 20241219

ACTIVE INGREDIENTS: HOMOSALATE 70 mg/1 mL; OCTINOXATE 50 mg/1 mL; OCTOCRYLENE 50 mg/1 mL; AVOBENZONE 20 mg/1 mL
INACTIVE INGREDIENTS: WATER; CETYL ALCOHOL; DICAPRYLYL CARBONATE; MEDIUM-CHAIN TRIGLYCERIDES; CHICORY LEAF; HEXYLENE GLYCOL; CAPRYLYL GLYCOL; GLYCERYL STEARATE SE; PHENOXYETHANOL; CETYL PALMITATE; HEXYLDECANOL; HEXYLDECYL LAURATE; SODIUM STEAROYL GLUTAMATE; GLYCERIN; SUNFLOWER OIL; CHLORELLA VULGARIS; ROSEMARY; NIACINAMIDE; POLYMETHYLSILSESQUIOXANE (4.5 MICRONS); EDETATE DISODIUM ANHYDROUS; XANTHAN GUM; ETHYLHEXYLGLYCERIN

Dr. C. Tuna Resurface Essential Day Cream SPF 30

Active Ingredient:

Homosalate 7%

Ethylhexyl Methoxycinnamate 5%

Octocrylene 5%

Butyl Methoxydibenzoylmethane 2%

Purpose

Sunscreen

Use:

Helps to moisturize and protect the skin from sun damage.

Warnings:

For external use only. Do not use on damaged or broken skin.

When using this product

keep out of eyes. Rinse with water to remove

Stop use and ask a doctor

if skin irritation develops when using this product. If swallowed, get medical help or contact a Poison Control Center right away.

Directions:

Use daily, every morning 15 minutes before sun exposure. Take enough amounts with the enclosed spatula on your hands; gently apply on clean face and neck.

INACTIVE INGREDIENTS:

Water/Aqua, Cetyl Alcohol, Dicaprylyl Carbonate, Caprylic/Capric Triglyceride, Cichorium Intybus Leaf Extract, Hexylene Glycol, Caprylyl Glycol, Glyceryl Stearate SE, Phenoxyethanol, Cetyl Palmitate, Hexyldecanol, Hexyldecyl Laurate, Sodium Stearoyl Glutamate, Glycerin, Sodium Polyacrylate, Helianthus Annuus Seed Oil, Chlorella Vulgaris Extract, Rosmarinus Officinalis Leaf Extract, Niacinamide, Polymethylsilsesquioxane, Disodium EDTA, Xanthan Gum, Ethylhexylglycerin.

Questions or Comments?

info@farmasius.com (833) 432-7627 Monday – Friday (9 a.m – 9 p.m. EST)